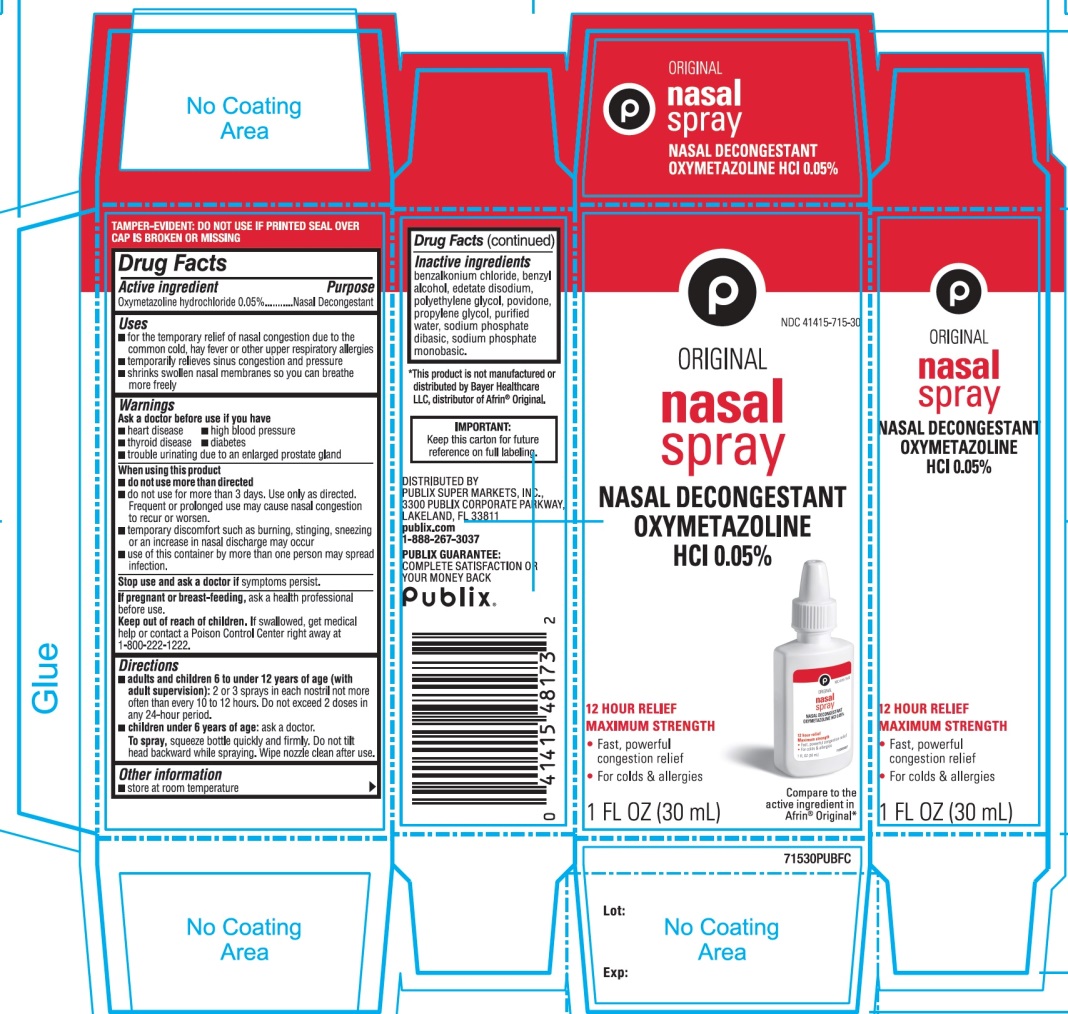 DRUG LABEL: Publix

NDC: 41415-715 | Form: SPRAY
Manufacturer: PUBLIX SUPER MARKETS, INC
Category: otc | Type: HUMAN OTC DRUG LABEL
Date: 20251028

ACTIVE INGREDIENTS: OXYMETAZOLINE HYDROCHLORIDE 0.05 g/100 mL
INACTIVE INGREDIENTS: BENZALKONIUM CHLORIDE; BENZYL ALCOHOL; EDETATE DISODIUM; POLYETHYLENE GLYCOL, UNSPECIFIED; POVIDONE, UNSPECIFIED; PROPYLENE GLYCOL; WATER; SODIUM PHOSPHATE, DIBASIC, UNSPECIFIED FORM; SODIUM PHOSPHATE, MONOBASIC, UNSPECIFIED FORM

Publix Nasal Oxymetazoline HCl Spray Drug Facts

Active ingredient

Oxymetazoline hydrochloride 0.05%

Purpose

Nasal Decongestant

Uses

- for the temporarily relief of nasal congestion due to the, common cold, hay fever or other upper respiratory allergies
- temporarily relieves sinus congestion and pressure
- shrinks swollen nasal membranes so you can breathe more freely

Ask a doctor before use if you have

- heart disease
- high blood pressure
- diabetes
- thyroid disease
- trouble urinating due to an enlarged prostate gland

When using this product

- do not use more than directed
- do not use for more than 3 days. Use only as directed. Frequent or prolonged use may cause nasal congestion to recur or worsen.
- temporary discomfort such as burning, stinging, sneezing or an increase in nasal discharge may occur
- use of this container by more than one person may spread infection

Stop use and ask a doctor if

symptoms persist

If pregnant or breast-feeding,

ask a health professional before use.

Keep out of reach of children.

If swallowed, get medical help or contact a Poison Control Center right away at (1-800-222-1222).

Directions

- adults and children 6 to under 12 years of age (with adult supervision):2 or 3 sprays in each nostril not more often than every 10 to 12 hours. Do not exceed 2 doses in any 24-hour period.
- children under 6 years of age:ask a doctor

To Spray:squeeze bottle quickly and firmly. Do not tilt head backward while spraying. Wipe nozzle clean after use. Secure cap after use.

Other information

- store at room temperature

Inactive ingredients

benzalkonium chloride, benzyl alcohol, edetate disodium, polyethylene glycol, povidone, propylene glycol, purified water, sodium phosphate dibasic, sodium phosphate monobasic.

Questions or comments?

1-866-467-2748

Principal Display Panel

Publix®

NDC# 41415-715-30

Compare to the active ingredient in Afrin® original*

ORIGINAL

Nasal Spray

NASAL DECONGESTANT

OXYMETAZOLINE HCL 0.05%

12 HOUR RELIEF

MAXIMUM STRENGTH

- Fast, Powerful Congestion Relief
- For Colds & Allergies

1 FL OZ (30 mL)

IMPORTANT:Keep this carton for future reference on full labeling.

DISTRIBUTED BY

PUBLIX SUPER MARKETS, INC.,

3300 PUBLIX CORPORATE PARKWAY,

LAKELAND, FL 33811

publix.com, 1-888-267-3037

PUBLIX GUARANTEE:COMPLETE SATISFACTION OR YOUR MONEY BACK.

*This product is not manufactured or distributed by Bayer Healthcare LLC, distributer of Afrin®Original.